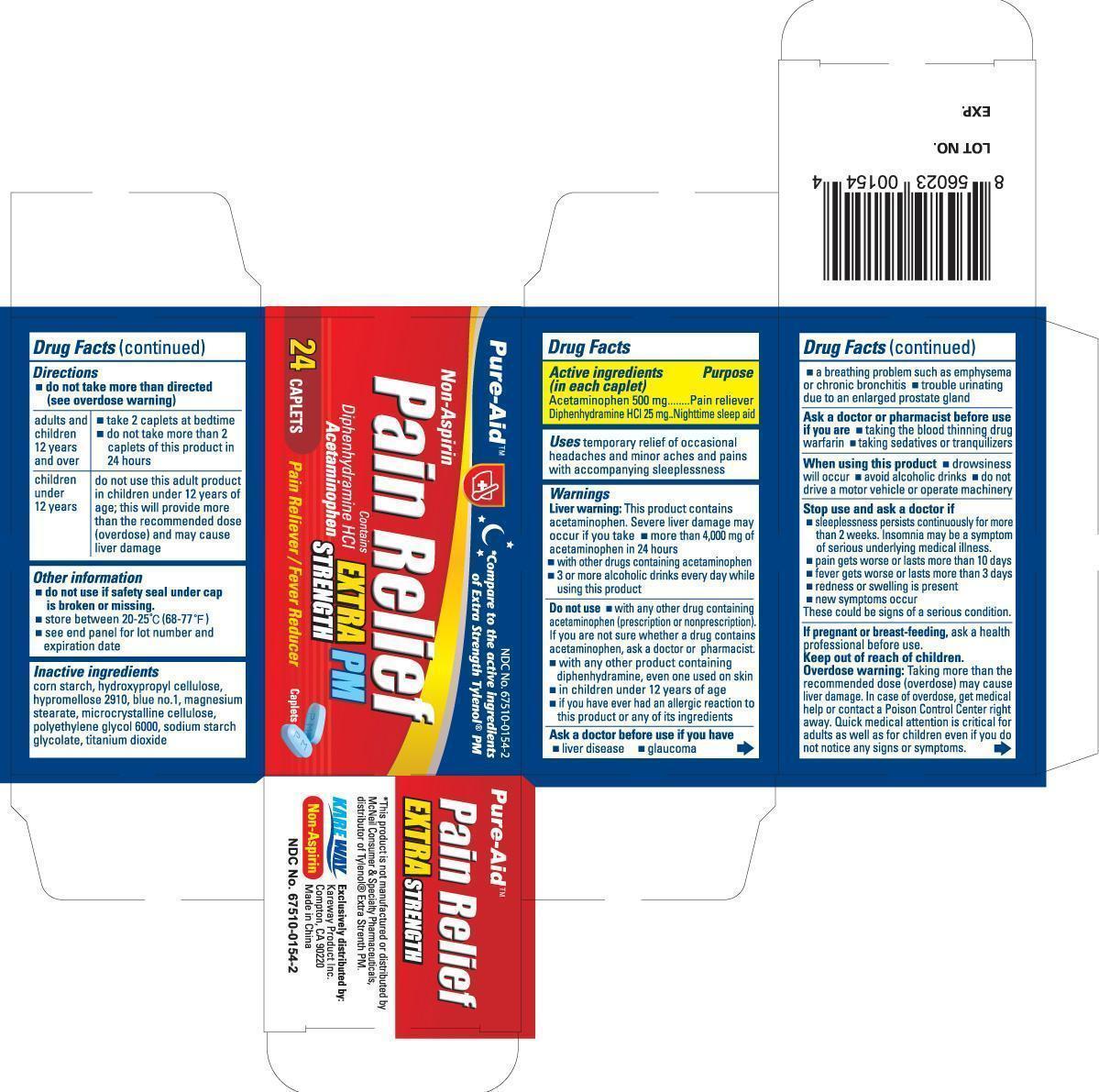 DRUG LABEL: Acetaminophen PM
NDC: 67510-0154 | Form: TABLET
Manufacturer: Kareway Product, Inc.
Category: otc | Type: HUMAN OTC DRUG LABEL
Date: 20130802

ACTIVE INGREDIENTS: ACETAMINOPHEN 500 mg/1 1; DIPHENHYDRAMINE HYDROCHLORIDE 25 mg/1 1
INACTIVE INGREDIENTS: STARCH, CORN; FD&C BLUE NO. 1; MAGNESIUM STEARATE; CELLULOSE, MICROCRYSTALLINE; POLYETHYLENE GLYCOL 6000; SODIUM STARCH GLYCOLATE TYPE A POTATO; TITANIUM DIOXIDE

Drug Facts

Active Ingredients (in each caplet)

Acetaminophen 500mg

Diphenhydramine HCl 25mg

Purpose

Pain reliever

Nighttime sleep aid

Uses

temporary relief of occasional headaches and minor aches and pains with accompanying sleeplessnes

Warnings

Liver warning:

This product contains acetaminophen. Severe liver damage may occur if you take

- more than 4,000ms of acetaminophen in 24 hours
- with other drugs containing acetaminophen
- 3 or more alcoholic drinks every day while using this product

Do not use

- with any other drug containing acetaminophen (prescription or nonprescription). If you are not sure whether a drug contains acetaminophen, ask a a doctor or pharmacist.
- with any other product containing diphenhydramine, even one used on skin
- in children under 12 years of age
- if you have ever had an allergic reaction to this product or any of its ingredients

Ask a doctor before use if you have

- liver disease
- glaucoma
- a breathing problem such as emphysema or chronic bronchitis
- trouble urinating due to an enlarged prostate gland

Ask a doctor or pharmacist before use if you are

- taking the blood thinning drug warfarin
- taking sedatives or tranquilizers

When using this product

- drowsiness will occur
- avoid alcoholic drinks
- do not drive a motor vehicle or operate machinery

Stop use and ask a doctor if

- sleeplessness persists continuously for more than 2 weeks. Insomnia may be a symptom of serious underlying medical illness
- pain gets worse or lasts more than 10 days
- redness or swelling is present
- new symptoms occur

These could be signs of a serious condition.

If pregnant or breast-feeding,

ask a health professional before use.

Keep out of reach of children.

Enter section text here

Overdose warning:

Taking more than the recommended dose (overdose) may cause liver damage. In case of overdose, get medical help or contact a Poison Control Center right away. Quick medical attention is critical for adults as well as for children even if you do not notice any signs or symptoms.

Directions

- Do not take more than directed (see overdose warning)

adults and children under 12 years and over | - take 2 caplets at bedtime - do not take more than 2 caplets of this product in 24 hours
children under 12 years | do not use this adult product in children under 12 years of age; this will provide more than the recommended dose (overdose) and may cause liver damage

Other information

- do not use if safety seal under cap is broken or missing
- store between 20-25°C (68-77°F)
- see end panel for lot number and expiration date

Inactive ingredients

corn starch, cydroxypropyl cellulose, hypromellose 2910, blue no.1, magnesium stearate, microcrystalline cellulose, polyethylene glycol 6000, sodium starch glycolate, titanium dioxide

PACKAGE LABEL

non-aspirin PM